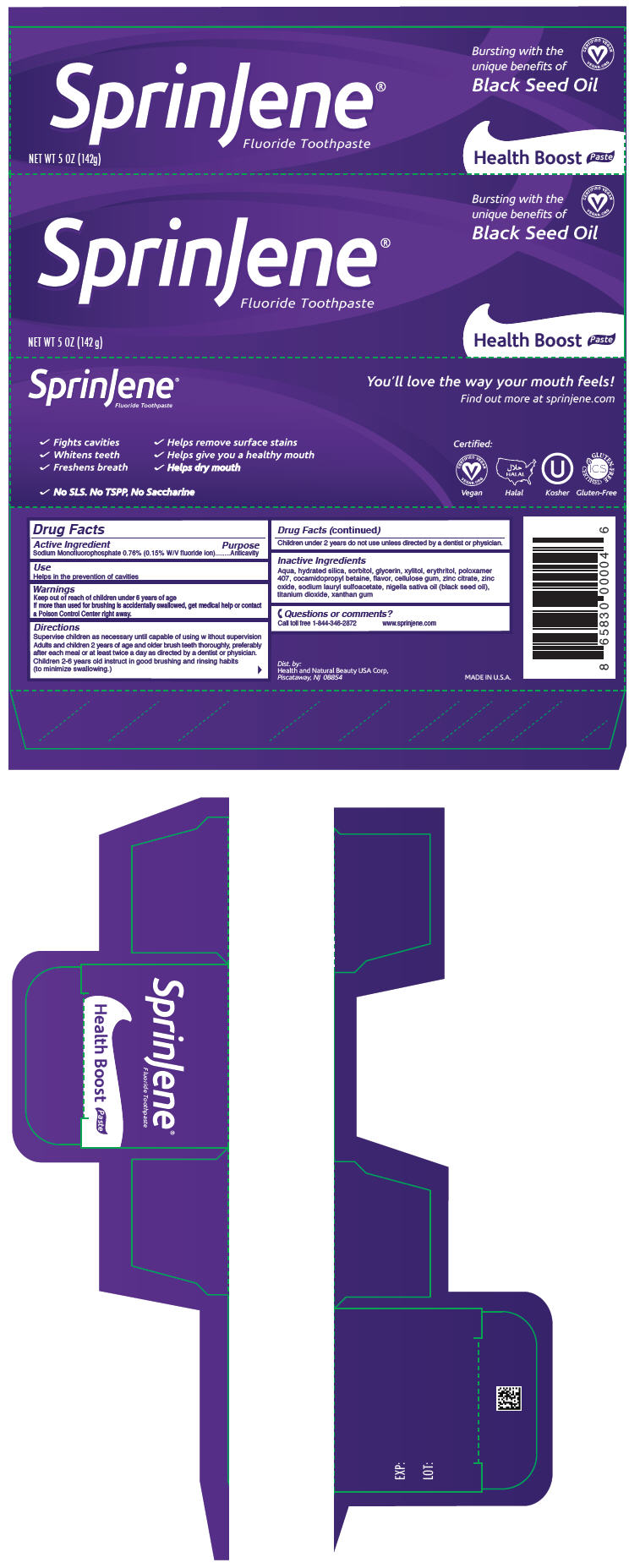 DRUG LABEL: SprinJene 
NDC: 63404-1108 | Form: PASTE, DENTIFRICE
Manufacturer: Health and Natural Beauty USA Corp
Category: otc | Type: HUMAN OTC DRUG LABEL
Date: 20230202

ACTIVE INGREDIENTS: Sodium Monofluorophosphate 1.5 mg/1 g
INACTIVE INGREDIENTS: Water; Hydrated Silica; Sorbitol; Glycerin; Xylitol; Erythritol; Poloxamer 407; Cocamidopropyl Betaine; Carboxymethylcellulose Sodium, Unspecified; Zinc Citrate; Zinc Oxide; Sodium Lauryl Sulfoacetate; Nigella Sativa Seed Oil; Titanium Dioxide; Xanthan Gum

SprinJene®
Health Boost

Drug Facts

Active Ingredient

Sodium Monofluorophosphate 0.76% (0.15% W/V fluoride ion)

Purpose

Anticavity

Use

Helps in the prevention of cavities

Warnings

Keep out of reach of children under 6 years of age

If more than used for brushing is accidentally swallowed, get medical help or contact a Poison Control Center right away.

Directions

Supervise children as necessary until capable of using w ithout supervision Adults and children 2 years of age and older brush teeth thoroughly, preferably after each meal or at least twice a day as directed by a dentist or physician.

Children 2-6 years old instruct in good brushing and rinsing habits (to minimize swallowing.)

Children under 2 years do not use unless directed by a dentist or physician.

Inactive Ingredients

Aqua, hydrated silica, sorbitol, glycerin, xylitol, erythritol, poloxamer 407, cocamidopropyl betaine, flavor, cellulose gum, zinc citrate, zinc oxide, sodium lauryl sulfoacetate, nigella sativa oil (black seed oil), titanium dioxide, xanthan gum

Questions or comments?

Call toll free 1-844-346-2872
www.sprinjene.com

Dist. by:
Health and Natural Beauty USA Corp,
Piscataway, NJ 08854

PRINCIPAL DISPLAY PANEL - 142 g Tube Carton

SprinJene®
Fluoride Toothpaste

NET WT 5 OZ (142g)

Bursting with the
unique benefits of
Black Seed Oil

CERTIFIED VEGAN
VEGAN.ORG

Health Boost Paste